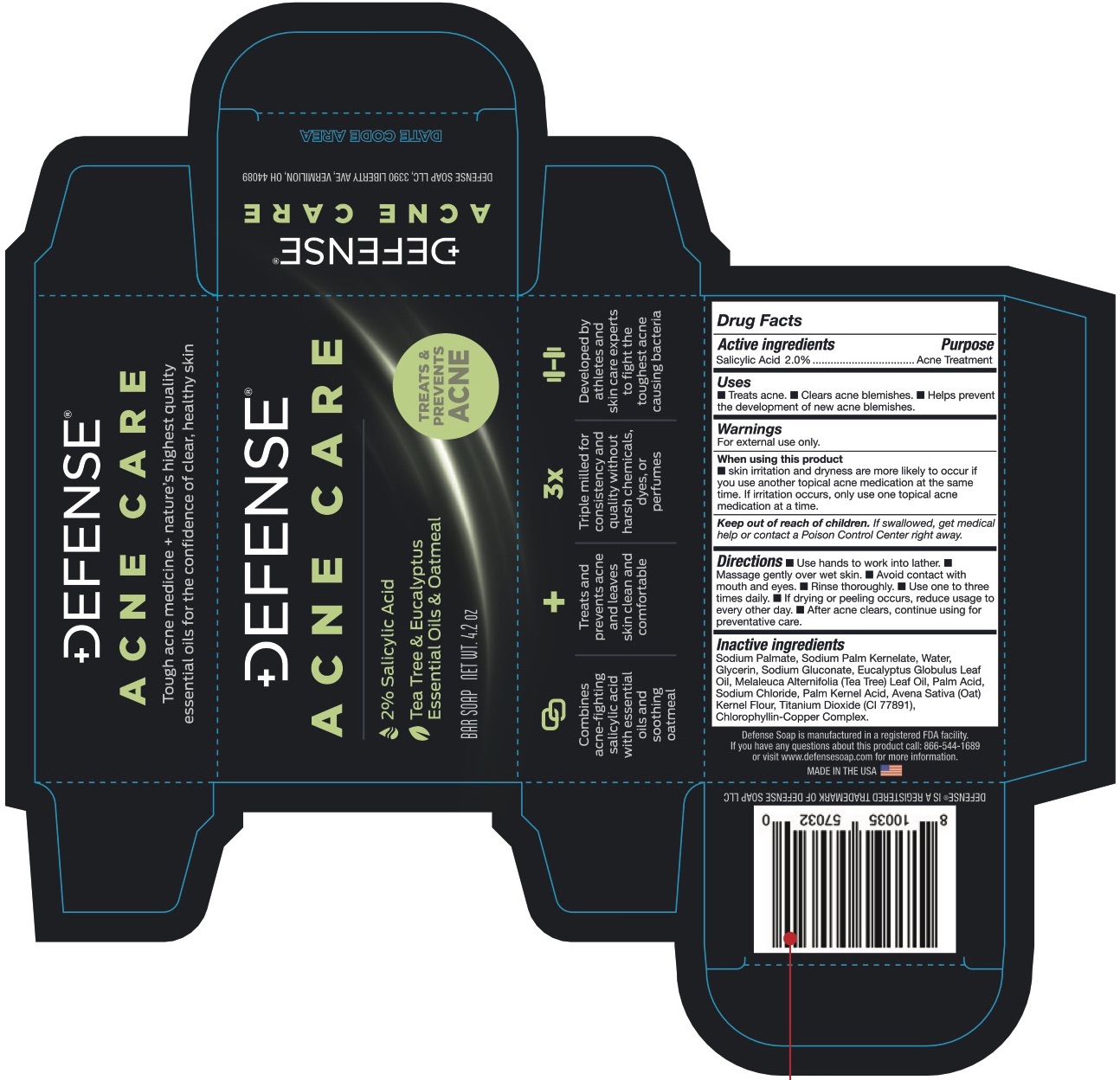 DRUG LABEL: Defense Acne Care 2% Salicylic Acid
NDC: 70856-3582 | Form: SOAP
Manufacturer: Defense Soap LLC
Category: otc | Type: HUMAN OTC DRUG LABEL
Date: 20251219

ACTIVE INGREDIENTS: SALICYLIC ACID 2 g/100 g
INACTIVE INGREDIENTS: SODIUM CHLORIDE; TITANIUM DIOXIDE; WATER; SODIUM GLUCONATE; EUCALYPTUS GLOBULUS LEAF; OATMEAL; SODIUM PALM KERNELATE; PALM ACID; SODIUM PALMATE; SODIUM COPPER CHLOROPHYLLIN; PALM KERNEL ACID; MELALEUCA ALTERNIFOLIA LEAF

Defense Acne Care 2% Salicylic Acid Soap

Drug Facts

Active ingredient

Salicylic acid 2%

Purpose

Acne treatment

Uses

- Treats acne.
- Clears acne blemishes.
- Helps prevent the development of new acne blemishes.

Warnings

For external use only

When using this product, skin irritation and dryness may occur if you use other topical acne medications at the same time. If irritation occurs, use only one medication at a time.

Keep out of reach of children. If swallowed, get medical help or contact a Poison Control Center right away.

Directions

- Use hands to work into a lather.
- Massage gently over wet skin.
- Avoid contact with mouth and eyes.
- Rinse thoroughly.
- Use one to three times daily
- If drying or peeling occurs, reduce usage to every other day.
- After acne clears, continue using for preventative care.

Inactive ingredients

Sodium Palmate, Sodium Palm Kernelate, Water, Sodium Gluconate, Eucalyptus Globulous Leaf Oil, Melaleuca Alternifolia (Tee Tree) Leaf Oil, Palm acid, Sodium chloride, Palm kernel acid, Avena Sativa (Oat) Kernel Flour, Titanium dioxide (CI77891), Chlorophyllin-Copper complex

Distributed by:

D3 Development, Inc., Portland, ME 04101

Made in the USA

PACKAGE LABEL

DEFENSE ACNE CARE

2% Salicylic Acid

Tea Tree & Eucalyptus Essential Oils & Oatmeal

Bar Soap

Net Wt. 4.2 oz